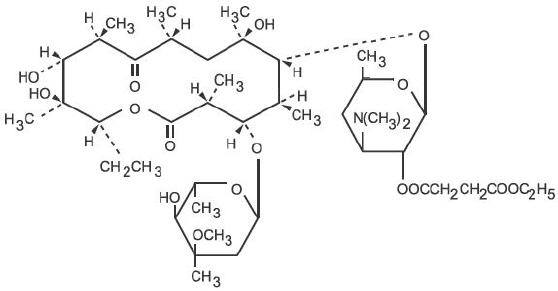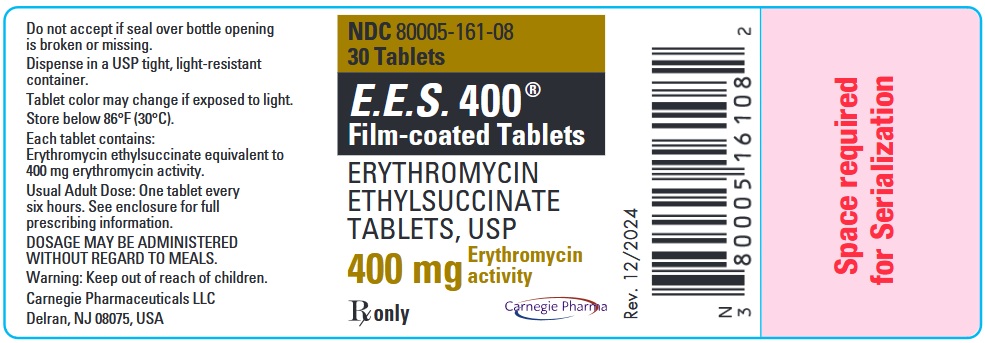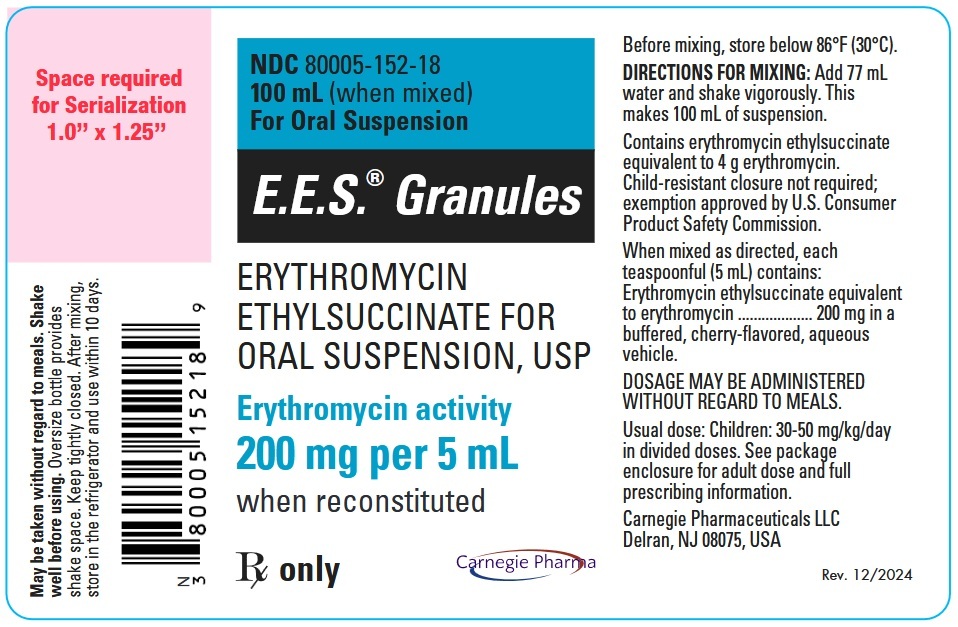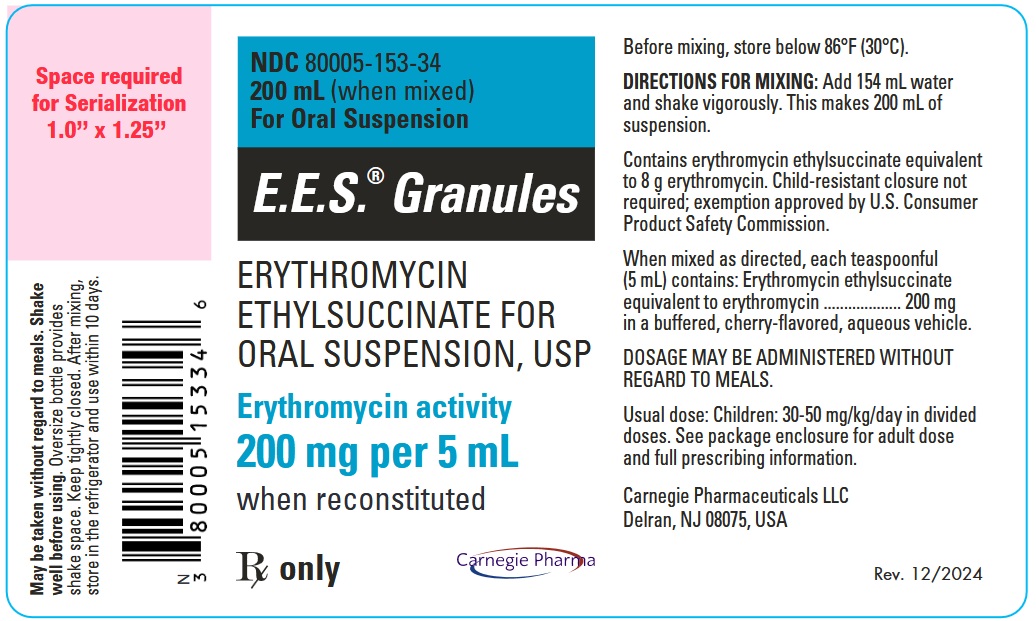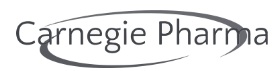 DRUG LABEL: E.E.S 

NDC: 80005-161 | Form: TABLET
Manufacturer: Carnegie Pharmaceuticals LLC
Category: prescription | Type: HUMAN PRESCRIPTION DRUG LABEL
Date: 20250221

ACTIVE INGREDIENTS: ERYTHROMYCIN ETHYLSUCCINATE 400 mg/1 1
INACTIVE INGREDIENTS: SUCROSE; STARCH, CORN; FD&C RED NO. 40; MAGNESIUM STEARATE; POLACRILIN POTASSIUM; SODIUM CITRATE, UNSPECIFIED FORM; D&C RED NO. 30; D&C YELLOW NO. 10; GLYCERYL MONOCAPRYLOCAPRATE; POLYVINYL ALCOHOL GRAFT POLYETHYLENE GLYCOL COPOLYMER (3:1; 45000 MW); POLYVINYL ALCOHOL, UNSPECIFIED; TALC; TITANIUM DIOXIDE

E.E.S.®
(ERYTHROMYCIN ETHYLSUCCINATE)

Rx only

To reduce the development of drug-resistant bacteria and maintain the effectiveness of E.E.S. and other antibacterial drugs, E.E.S. should be used only to treat or prevent infections that are proven or strongly suspected to be caused by bacteria.

DESCRIPTION

Erythromycin is produced by a strain of Saccharopolyspora erythraea (formerly Streptomyces erythraeus) and belongs to the macrolide group of antibiotics. It is basic and readily forms salts with acids. The base, the stearate salt, and the esters are poorly soluble in water. Erythromycin ethylsuccinate is an ester of erythromycin suitable for oral administration. Erythromycin ethylsuccinate is known chemically as erythromycin 2'-(ethylsuccinate). The molecular formula is C43H75NO16 and the molecular weight is 862.06. The structural formula is:

E.E.S. Granules are intended for reconstitution with water. Each 5-mL teaspoonful of reconstituted cherry-flavored suspension contains erythromycin ethylsuccinate equivalent to 200 mg of erythromycin.

The pleasant tasting, fruit-flavored liquids are supplied ready for oral administration.

E.E.S. 200 Liquid: Each 5-mL teaspoonful of fruit-flavored suspension contains erythromycin ethylsuccinate equivalent to 200 mg of erythromycin.

E.E.S. 400 Liquid: Each 5-mL teaspoonful of orange-flavored suspension contains erythromycin ethylsuccinate equivalent to 400 mg of erythromycin.

Granules and ready-made suspensions are intended primarily for pediatric use but can also be used in adults.

E.E.S. 400 film-coated tablets: Each tablet contains erythromycin ethylsuccinate equivalent to 400 mg of erythromycin.

The film-coated tablets are intended primarily for adults or older children.

Inactive Ingredients:

E.E.S. Granules: Citric acid, FD&C Red No. 3, magnesium aluminum silicate, sodium carboxymethylcellulose, sodium citrate, sucrose and artificial flavor.

E.E.S. 400 film-coated tablets: Confectioner's sugar (contains corn starch), corn starch, FD&C Red No. 40, magnesium stearate, polacrilin potassium, sodium citrate and Opadry® Pink 321A140035 (consists of the following ingredients: D&C Red #30, D&C Yellow #10, glycerol monocaprylocaprate, Macrogol (PEG) Polyvinyl Alcohol Graft Copolymer, polyvinyl alcohol partially hydrolyzed, talc and titanium dioxide).

E.E.S. 200 Liquid: FD&C Red No. 40, methylparaben, polysorbate 60, propylparaben, sodium citrate, sucrose, water, xanthan gum and natural and artificial flavors.

E.E.S. 400 Liquid: D&C Yellow No. 10, FD&C Yellow No. 6, methylparaben, polysorbate 60, propylparaben, sodium citrate, sucrose, water, xanthan gum and natural and artificial flavors.

CLINICAL PHARMACOLOGY

Orally administered erythromycin ethylsuccinate suspensions and film-coated tablets are readily and reliably absorbed. Comparable serum levels of erythromycin are achieved in the fasting and nonfasting states.

Erythromycin diffuses readily into most body fluids. Only low concentrations are normally achieved in the spinal fluid, but passage of the drug across the blood-brain barrier increases in meningitis. In the presence of normal hepatic function, erythromycin is concentrated in the liver and excreted in the bile; the effect of hepatic dysfunction on excretion of erythromycin by the liver into the bile is not known. Less than 5 percent of the orally administered dose of erythromycin is excreted in active form in the urine.

Erythromycin crosses the placental barrier, but fetal plasma levels are low. The drug is excreted in human milk.

Microbiology

Mechanism of Action

Erythromycin acts by inhibition of protein synthesis by binding 50S ribosomal subunits of susceptible organisms. It does not affect nucleic acid synthesis.

Resistance

The major route of resistance is modification of the 23S rRNA in the 50S ribosomal subunit to insensitivity while efflux can also be significant.

Interactions With Other Antimicrobials

Antagonism exists in vitro between erythromycin and clindamycin, lincomycin, and chloramphenicol.

Antimicrobial Activity

Erythromycin has been shown to be active against most isolates of the following microorganisms both in vitro and in clinical infections [see Indications and Usage (1)].

Aerobic bacteria

Gram-positive bacteria:

Corynebacterium diphtheriae
Corynebacterium minutissimum
Listeria monocytogenes
Staphylococcus aureus (resistant organisms may emerge during treatment)
Streptococcus pneumoniae
Streptococcus pyogenes

Gram-negative bacteria:

Bordetella pertussis
Haemophilus influenzae
Legionella pneumophila
Neisseria gonorrhoeae

Other microorganisms:

Chlamydia trachomatis
Entamoeba histolytica
Mycoplasma pneumoniae
Treponema pallidum
Ureaplasma urealyticum

The following in vitro data are available, but their clinical significance is unknown. At least 90 percent of the following bacteria exhibit in vitro minimum inhibitory concentration (MIC) less than or equal to the susceptible breakpoint for erythromycin against isolates of similar genus or organism group. However, the efficacy of erythromycin in treating clinical infections caused by these bacteria has not been established in adequate and well-controlled clinical trials.

Aerobic bacteria

Gram-positive bacteria:

Viridans group streptococci

Gram-negative bacteria:

Moraxella catarrhalis

Susceptibility Testing

For specific information regarding susceptibility test interpretive criteria and associated test methods and quality control standards recognized by FDA for this drug, please see: https://www.fda.gov/STIC.

INDICATIONS AND USAGE

To reduce the development of drug-resistant bacteria and maintain the effectiveness of E.E.S. and other antibacterial drugs, E.E.S. should be used only to treat or prevent infections that are proven or strongly suspected to be caused by susceptible bacteria. When culture and susceptibility information are available, they should be considered in selecting or modifying antibacterial therapy. In the absence of such data, local epidemiology and susceptibility patterns may contribute to the empiric selection of therapy.

E.E.S. is indicated in the treatment of infections caused by susceptible strains of the designated organisms in the diseases listed below:

Upper respiratory tract infections of mild to moderate degree caused by Streptococcus pyogenes, Streptococcus pneumoniae, or Haemophilus influenzae (when used concomitantly with adequate doses of sulfonamides, since many strains of H. influenzae are not susceptible to the erythromycin concentrations ordinarily achieved). (See appropriate sulfonamide labeling for prescribing information.)

Lower-respiratory tract infections of mild to moderate severity caused by Streptococcus pneumoniae or Streptococcus pyogenes.

Listeriosis caused by Listeria monocytogenes.

Pertussis (whooping cough) caused by Bordetella pertussis. Erythromycin is effective in eliminating the organism from the nasopharynx of infected individuals rendering them noninfectious. Some clinical studies suggest that erythromycin may be helpful in the prophylaxis of pertussis in exposed susceptible individuals.

Respiratory tract infections due to Mycoplasma pneumoniae.

Skin and skin structure infections of mild to moderate severity caused by Streptococcus pyogenes or Staphylococcus aureus (resistant staphylococci may emerge during treatment).

Diphtheria: Infections due to Corynebacterium diphtheriae, as an adjunct to antitoxin, to prevent establishment of carriers and to eradicate the organism in carriers.

Erythrasma: In the treatment of infections due to Corynebacterium minutissimum.

Intestinal amebiasis caused by Entamoeba histolytica (oral erythromycins only). Extraenteric amebiasis requires treatment with other agents.

Acute pelvic inflammatory disease caused by Neisseria gonorrhoeae: As an alternative drug in treatment of acute pelvic inflammatory disease caused by N. gonorrhoeae in female patients with a history of sensitivity to penicillin. Patients should have a serologic test for syphilis before receiving erythromycin as treatment of gonorrhea and a follow-up serologic test for syphilis after 3 months.

Syphilis caused by Treponema pallidum: Erythromycin is an alternate choice of treatment for primary syphilis in patients allergic to the penicillins. In treatment of primary syphilis, spinal fluid examinations should be done before treatment and as part of follow-up after therapy.

Erythromycins are indicated for the treatment of the following infections caused by Chlamydia trachomatis: conjunctivitis of the newborn, pneumonia of infancy, and urogenital infections during pregnancy. When tetracyclines are contraindicated or not tolerated, erythromycin is indicated for the treatment of uncomplicated urethral, endocervical, or rectal infections in adults due to Chlamydia trachomatis.

When tetracyclines are contraindicated or not tolerated, erythromycin is indicated for the treatment of nongonococcal urethritis caused by Ureaplasma urealyticum.

Legionnaires' Disease caused by Legionella pneumophila: Although no controlled clinical efficacy studies have been conducted, in vitro and limited preliminary clinical data suggest that erythromycin may be effective in treating Legionnaires' Disease.

Prophylaxis:

Prevention of Initial Attacks of Rheumatic Fever

Penicillin is considered by the American Heart Association to be the drug of choice in the prevention of initial attacks of rheumatic fever (treatment of Streptococcus pyogenes infections of the upper respiratory tract, e.g., tonsillitis or pharyngitis). Erythromycin is indicated for the treatment of penicillin-allergic patients.^1

The therapeutic dose should be administered for 10 days.

Prevention of Recurrent Attacks of Rheumatic Fever

Penicillin or sulfonamides are considered by the American Heart Association to be the drugs of choice in the prevention of recurrent attacks of rheumatic fever. In patients who are allergic to penicillin and sulfonamides, oral erythromycin is recommended by the American Heart Association in the long-term prophylaxis of streptococcal pharyngitis (for the prevention of recurrent attacks of rheumatic fever).^1

CONTRAINDICATIONS

Erythromycin is contraindicated in patients with known hypersensitivity to this antibiotic.

Erythromycin is contraindicated in patients taking terfenadine, astemizole, pimozide, or cisapride (see PRECAUTIONS – Drug Interactions).

Do not use erythromycin concomitantly with HMG CoA reductase inhibitors (statins) that are extensively metabolized by CYP 3A4 (lovastatin or simvastatin), due to the increased risk of myopathy, including rhabdomyolysis.

WARNINGS

Hepatotoxicity

There have been reports of hepatic dysfunction, including increased liver enzymes, and hepatocellular and/or cholestatic hepatitis, with or without jaundice, occurring in patients receiving oral erythromycin products.

QT Prolongation

Erythromycin has been associated with prolongation of the QT interval and infrequent cases of arrhythmia. Cases of torsades de pointes have been spontaneously reported during postmarketing surveillance in patients receiving erythromycin. Fatalities have been reported. Erythromycin should be avoided in patients with known prolongation of the QT interval, patients with ongoing proarrhythmic conditions such as uncorrected hypokalemia or hypomagnesemia, clinically significant bradycardia, and in patients receiving Class IA (quinidine, procainamide) or Class III (dofetilide, amiodarone, sotalol) antiarrhythmic agents. Elderly patients may be more susceptible to drug-associated effects on the QT interval.

Syphilis in Pregnancy

There have been reports suggesting that erythromycin does not reach the fetus in adequate concentration to prevent congenital syphilis. Infants born to women treated during pregnancy with oral erythromycin for early syphilis should be treated with an appropriate penicillin regimen.

Clostridium difficile Associated Diarrhea

Clostridium difficile associated diarrhea (CDAD) has been reported with use of nearly all antibacterial agents, including E.E.S., and may range in severity from mild diarrhea to fatal colitis. Treatment with antibacterial agents alters the normal flora of the colon leading to overgrowth of C. difficile.

C. difficile produces toxins A and B which contribute to the development of CDAD. Hypertoxin producing strains of C. difficile cause increased morbidity and mortality, as these infections can be refractory to antimicrobial therapy and may require colectomy. CDAD must be considered in all patients who present with diarrhea following antibiotic use. Careful medical history is necessary since CDAD has been reported to occur over two months after the administration of antibacterial agents.

If CDAD is suspected or confirmed, ongoing antibiotic use not directed against C. difficile may need to be discontinued. Appropriate fluid and electrolyte management, protein supplementation, antibiotic treatment of C. difficile, and surgical evaluation should be instituted as clinically indicated.

Drug Interactions

Serious adverse reactions have been reported in patients taking erythromycin concomitantly with CYP3A4 substrates. These include colchicine toxicity with colchicine; rhabdomyolysis with simvastatin, lovastatin, and atorvastatin; and hypotension with calcium channel blockers metabolized by CYP3A4 (e.g., verapamil, amlodipine, diltiazem) (see PRECAUTIONS – Drug Interactions).

There have been post-marketing reports of colchicine toxicity with concomitant use of erythromycin and colchicine. This interaction is potentially life-threatening, and may occur while using both drugs at their recommended doses (see PRECAUTIONS – Drug Interactions).

Rhabdomyolysis with or without renal impairment has been reported in seriously ill patients receiving erythromycin concomitantly with lovastatin. Therefore, patients receiving concomitant lovastatin and erythromycin should be carefully monitored for creatine kinase (CK) and serum transaminase levels. (See package insert for lovastatin.)

PRECAUTIONS

General

Prescribing E.E.S. in the absence of a proven or strongly suspected bacterial infection or a prophylactic indication is unlikely to provide benefit to the patient and increases the risk of the development of drug-resistant bacteria.

Since erythromycin is principally excreted by the liver, caution should be exercised when erythromycin is administered to patients with impaired hepatic function (see CLINICAL PHARMACOLOGY and WARNINGS sections).

Exacerbation of symptoms of myasthenia gravis and new onset of symptoms of myasthenic syndrome have been reported in patients receiving erythromycin therapy.

There have been reports of infantile hypertrophic pyloric stenosis (IHPS) occurring in infants following erythromycin therapy. In one cohort of 157 newborns who were given erythromycin for pertussis prophylaxis, seven neonates (5%) developed symptoms of non-bilious vomiting or irritability with feeding and were subsequently diagnosed as having IHPS requiring surgical pyloromyotomy. A possible dose-response effect was described with an absolute risk of IHPS of 5.1% for infants who took erythromycin for 8 to 14 days and 10% for infants who took erythromycin for 15 to 21 days.^2

Since erythromycin may be used in the treatment of conditions in infants which are associated with significant mortality or morbidity (such as pertussis or neonatal Chlamydia trachomatis infections), the benefit of erythromycin therapy needs to be weighed against the potential risk of developing IHPS. Parents should be informed to contact their physician if vomiting or irritability with feeding occurs.

Prolonged or repeated use of erythromycin may result in an overgrowth of nonsusceptible bacteria or fungi. If superinfection occurs, erythromycin should be discontinued and appropriate therapy instituted.

When indicated, incision and drainage or other surgical procedures should be performed in conjunction with antibiotic therapy.

Information for Patients

Patients should be counseled that antibacterial drugs, including E.E.S., should only be used to treat bacterial infections. They do not treat viral infections (e.g., the common cold). When E.E.S. is prescribed to treat a bacterial infection, patients should be told that although it is common to feel better early in the course of therapy, the medication should be taken exactly as directed. Skipping doses or not completing the full course of therapy may (1) decrease the effectiveness of the immediate treatment and (2) increase the likelihood that bacteria will develop resistance and will not be treatable by E.E.S. or other antibacterial drugs in the future.

Diarrhea is a common problem caused by antibiotics which usually ends when the antibiotic is discontinued. Sometimes after starting treatment with antibiotics, patients can develop watery and bloody stools (with or without stomach cramps and fever) even as late as two or more months after having taken the last dose of the antibiotic. If this occurs, patients should contact their physician as soon as possible.

Drug Interactions

Theophylline

Erythromycin use in patients who are receiving high doses of theophylline may be associated with an increase in serum theophylline levels and potential theophylline toxicity. In case of theophylline toxicity and/or elevated serum theophylline levels, the dose of theophylline should be reduced while the patient is receiving concomitant erythromycin therapy.

There have been published reports suggesting that when oral erythromycin is given concurrently with theophylline there is a decrease in erythromycin serum concentrations of approximately 35%. The mechanism by which this interaction occurs is unknown. The decrease in erythromycin concentrations due to co-administration of theophylline could result in subtherapeutic concentrations of erythromycin.

Verapamil

Hypotension, bradyarrhythmias, and lactic acidosis have been observed in patients receiving concurrent verapamil, belonging to the calcium channel blockers drug class.

Digoxin

Concomitant administration of erythromycin and digoxin has been reported to result in elevated digoxin serum levels.

Anticoagulants

There have been reports of increased anticoagulant effects when erythromycin and oral anticoagulants were used concomitantly. Increased anticoagulation effects due to interactions of erythromycin with various oral anticoagulants may be more pronounced in the elderly.

Erythromycin is a substrate and inhibitor of the 3A isoform subfamily of the cytochrome p450 enzyme system (CYP3A). Coadministration of erythromycin and a drug primarily metabolized by CYP3A may be associated with elevations in drug concentrations that could increase or prolong both the therapeutic and adverse effects of the concomitant drug. Dosage adjustments may be considered, and when possible, serum concentrations of drugs primarily metabolized by CYP3A should be monitored closely in patients concurrently receiving erythromycin.

The following are examples of some clinically significant CYP3A based drug interactions. Interactions with other drugs metabolized by the CYP3A isoform are also possible. The following CYP3A based drug interactions have been observed with erythromycin products in post-marketing experience:

Ergotamine/dihydroergotamine

Post-marketing reports indicate that coadministration of erythromycin with ergotamine or dihydroergotamine has been associated with acute ergot toxicity characterized by vasospasm and ischemia of the extremities and other tissues including the central nervous system. Concomitant administration of erythromycin with ergotamine or dihydroergotamine is contraindicated (see CONTRAINDICATIONS).

Triazolobenzodiazepines (such as triazolam and alprazolam) and related benzodiazepines

Erythromycin has been reported to decrease the clearance of triazolam and midazolam, and thus, may increase the pharmacologic effect of these benzodiazepines.

HMG-CoA Reductase Inhibitors

Erythromycin has been reported to increase concentrations of HMG-CoA reductase inhibitors (e.g., lovastatin and simvastatin). Rare reports of rhabdomyolysis have been reported in patients taking these drugs concomitantly.

Sildenafil (Viagra)

Erythromycin has been reported to increase the systemic exposure (AUC) of sildenafil. Reduction of sildenafil dosage should be considered. (See Viagra package insert.)

There have been spontaneous or published reports of CYP3A based interactions of erythromycin with cyclosporine, carbamazepine, tacrolimus, alfentanil, disopyramide, rifabutin, quinidine, methylprednisolone, cilostazol, vinblastine, and bromocriptine.

Concomitant administration of erythromycin with cisapride, pimozide, astemizole, or terfenadine is contraindicated (see CONTRAINDICATIONS).

In addition, there have been reports of interactions of erythromycin with drugs not thought to be metabolized by CYP3A, including hexobarbital, phenytoin, and valproate.

Erythromycin has been reported to significantly alter the metabolism of the nonsedating antihistamines terfenadine and astemizole when taken concomitantly. Rare cases of serious cardiovascular adverse events, including electrocardiographic QT/QTc interval prolongation, cardiac arrest, torsades de pointes, and other ventricular arrhythmias have been observed (see CONTRAINDICATIONS). In addition, deaths have been reported rarely with concomitant administration of terfenadine and erythromycin.

There have been post-marketing reports of drug interactions when erythromycin is co-administered with cisapride, resulting in QT prolongation, cardiac arrhythmias, ventricular tachycardia, ventricular fibrillation, and torsades de pointes, most likely due to inhibition of hepatic metabolism of cisapride by erythromycin. Fatalities have been reported (see CONTRAINDICATIONS).

Colchicine

Colchicine is a substrate for both CYP3A4 and the efflux transporter P-glycoprotein (P-gp). Erythromycin is considered a moderate inhibitor of CYP3A4. A significant increase in colchicine plasma concentration is anticipated when co-administered with moderate CYP3A4 inhibitors such as erythromycin. If co-administration of colchicine and erythromycin is necessary, the starting dose of colchicine may need to be reduced, and the maximum colchicine dose should be lowered. Patients should be monitored for clinical symptoms of colchicine toxicity (see WARNINGS).

Drug/Laboratory Test Interactions:

Erythromycin interferes with the fluorometric determination of urinary catecholamines.

Carcinogenesis, Mutagenesis, Impairment of Fertility:

Long-term oral dietary studies conducted with erythromycin stearate in rats up to 400 mg/kg/day and in mice up to about 500 mg/kg/day (approximately 1 to 2 fold of the maximum human dose on a body surface area basis) did not provide evidence of tumorigenicity. Erythromycin stearate did not show genotoxic potential in the Ames, and mouse lymphoma assays or induce chromosomal aberrations in CHO cells. There was no apparent effect on male or female fertility in rats treated with erythromycin base by oral gavage at 700 mg/kg/day (approximately 3 times the maximum human dose on a body surface area basis).

Pregnancy:

Teratogenic Effects

There is no evidence of teratogenicity or any other adverse effect on reproduction in female rats fed erythromycin base by oral gavage at 350 mg/kg/day (approximately twice the maximum recommended human dose on a body surface area) prior to and during mating, during gestation, and through weaning.

No evidence of teratogenicity or embryotoxicity was observed when erythromycin base was given by oral gavage to pregnant rats and mice at 700 mg/kg/day and to pregnant rabbits at 125 mg/kg/day (approximately 1 to 3 times the maximum recommended human dose).

Labor and Delivery:

The effect of erythromycin on labor and delivery is unknown.

Nursing Mothers:

Erythromycin is excreted in human milk. Caution should be exercised when erythromycin is administered to a nursing woman.

Pediatric Use:

See INDICATIONS AND USAGE and DOSAGE AND ADMINISTRATION sections.

Geriatric Use:

Elderly patients, particularly those with reduced renal or hepatic function, may be at increased risk for developing erythromycin-induced hearing loss (see ADVERSE REACTIONS and DOSAGE AND ADMINISTRATION).

Elderly patients may be more susceptible to the development of torsades de pointes arrhythmias than younger patients (see WARNINGS).

Elderly patients may experience increased effects of oral anticoagulant therapy while undergoing treatment with erythromycin (see PRECAUTIONS – Drug Interactions).

E.E.S.® Granules contains 25.9 mg (1.1 mEq) of sodium per individual dose.

The geriatric population may respond with a blunted natriuresis to salt loading. This may be clinically important with regard to such diseases as congestive heart failure.

E.E.S. 400 film-coated contains 47 mg (2 mEq) of sodium per tablet and 10.0 mg (0.3 mEq) of potassium per tablet.

ADVERSE REACTIONS

The most frequent side effects of oral erythromycin preparations are gastrointestinal and are dose-related. They include nausea, vomiting, abdominal pain, diarrhea and anorexia. Symptoms of hepatitis, hepatic dysfunction and/or abnormal liver function test results may occur (see WARNINGS section).

Onset of pseudomembranous colitis symptoms may occur during or after antibacterial treatment (see WARNINGS section).

Erythromycin has been associated with QT prolongation and ventricular arrhythmias, including ventricular tachycardia and torsades de pointes (see WARNINGS).

Allergic reactions ranging from urticaria to anaphylaxis have occurred. Skin reactions ranging from mild eruptions to erythema multiforme, Stevens-Johnson syndrome, and toxic epidermal necrolysis have been reported rarely.

There have been reports of interstitial nephritis coincident with erythromycin use.

There have been rare reports of pancreatitis and convulsions.

There have been isolated reports of reversible hearing loss occurring chiefly in patients with renal insufficiency and in patients receiving high doses of erythromycin.

OVERDOSAGE

In case of overdosage, erythromycin should be discontinued. Overdosage should be handled with the prompt elimination of unabsorbed drug and all other appropriate measures should be instituted.

Erythromycin is not removed by peritoneal dialysis or hemodialysis.

DOSAGE AND ADMINISTRATION

Erythromycin ethylsuccinate suspensions and film-coated tablets may be administered without regard to meals.

Children

Age, weight, and severity of the infection are important factors in determining the proper dosage. In mild to moderate infections, the usual dosage of erythromycin ethylsuccinate for children is 30 to 50 mg/kg/day in equally divided doses every 6 hours. For more severe infections, this dosage may be doubled. If twice-a-day dosage is desired, one-half of the total daily dose may be given every 12 hours. Doses may also be given three times daily by administering one-third of the total daily dose every 8 hours.

The following dosage schedule is suggested for mild to moderate infections:

Body Weight | Total Daily Dose
Under 10 lbs | 30 to 50 mg/kg/day 15 to 25 mg/lb/day
10 to 15 lbs | 200 mg
16 to 25 lbs | 400 mg
26 to 50 lbs | 800 mg
51 to 100 lbs | 1200 mg
over 100 lbs | 1600 mg

Adults

400 mg erythromycin ethylsuccinate every 6 hours is the usual dose. Dosage may be increased up to 4 g per day according to the severity of the infection. If twice-a-day dosage is desired, one-half of the total daily dose may be given every 12 hours. Doses may also be given three times daily by administering one-third of the total daily dose every 8 hours.

For adult dosage calculation, use a ratio of 400 mg of erythromycin activity as the ethylsuccinate to 250 mg of erythromycin activity as the stearate, base or estolate.

In the treatment of streptococcal infections, a therapeutic dosage of erythromycin ethylsuccinate should be administered for at least 10 days. In continuous prophylaxis against recurrences of streptococcal infections in persons with a history of rheumatic heart disease, the usual dosage is 400 mg twice a day.

For Treatment of Urethritis Due to C. trachomatis or U. urealyticum

800 mg three times a day for 7 days.

For Treatment of Primary Syphilis

Adults: 48 to 64 g given in divided doses over a period of 10 to 15 days.

For Intestinal Amebiasis

Adults: 400 mg four times daily for 10 to 14 days.

Children: 30 to 50 mg/kg/day in divided doses for 10 to 14 days.

For Use in Pertussis

Although optimal dosage and duration have not been established, doses of erythromycin utilized in reported clinical studies were 40 to 50 mg/kg/day, given in divided doses for 5 to 14 days.

For Treatment of Legionnaires' Disease

Although optimal doses have not been established, doses utilized in reported clinical data were those recommended above (1.6 to 4 g daily in divided doses).

Directions for Mixing E.E.S. Granules

100 mL

Add 77 mL water and shake vigorously. This makes 100 mL of suspension.

200 mL

Add 154 mL water and shake vigorously. This makes 200 mL of suspension.

HOW SUPPLIED

E.E.S. Granules 200 mg per 5 mL (erythromycin ethylsuccinate for oral suspension, USP) are pink granules with a cherry aroma and are supplied in
100-mL (NDC 80005-152-18) and 200-mL (NDC 80005-153-34) size bottles. Following reconstitution E.E.S. Granules become a pink opaque suspension with a cherry aroma.

E.E.S. 400 film-coated tablets (erythromycin ethylsuccinate tablets, USP) 400 mg, are supplied as pink oval tablets imprinted with the two letter
designation, EE, in:

Bottles of 30 (NDC 80005-161-08)
Bottles of 100 (NDC 80005-162-11)

Recommended Storage:

Store below 86°F (30°C).

Store granules, before mixing, below 86°F (30°C). After mixing, store in the refrigerator and use within 10 days.

REFERENCES

1. Committee on Rheumatic Fever, Endocarditis, and Kawasaki Disease of the Council on Cardiovascular Disease in the Young, the American Heart Association: Prevention of Rheumatic Fever. Circulation. 78(4):1082-1086, October 1988.
2. Honein, M.A., et al.: Infantile hypertrophic pyloric stenosis after pertussis prophylaxis with erythromycin: a case review and cohort study. The Lancet 1999:354 (9196): 2101-5.

Rev. 02/2025

Carnegie Pharmaceuticals LLC
Delran, NJ 08075, USA

PRINCIPAL DISPLAY PANEL - 400 mg Tablet Bottle Label

NDC 80005-161-08

30 Tablets

E.E.S.400®
Film-coated Tablets

ERYTHROMYCIN
ETHYLSUCCINATE
TABLETS, USP

400 mg
Erythromycin
activity

Rx only

Carnegie Pharma

PRINCIPAL DISPLAY PANEL - 100 mL Bottle Label

NDC 80005-152-18

100 mL(when mixed)

For Oral Suspension

E.E.S.® Granules

ERYTHROMYCIN
ETHYLSUCCINATE FOR
ORAL SUSPENSION, USP

Erythromycin activity
200 mg per 5 mL
when reconstituted

Rx only

Carnegie Pharma

PRINCIPAL DISPLAY PANEL - 5 mL Bottle Label

NDC 80005-153-34)

200 mL(when mixed)

For Oral Suspension

E.E.S.® Granules

ERYTHROMYCIN
ETHYLSUCCINATE FOR
ORAL SUSPENSION, USP

Erythromycin activity
200 mg per 5 mL
when reconstituted

Rx only